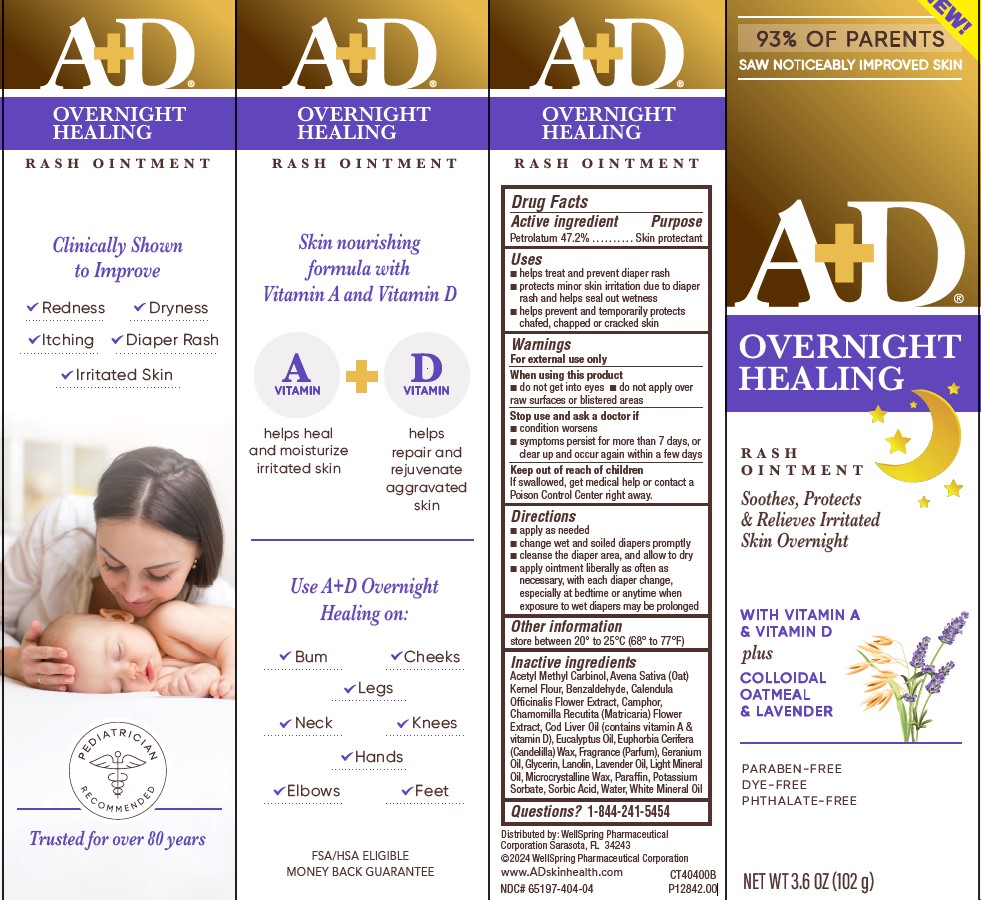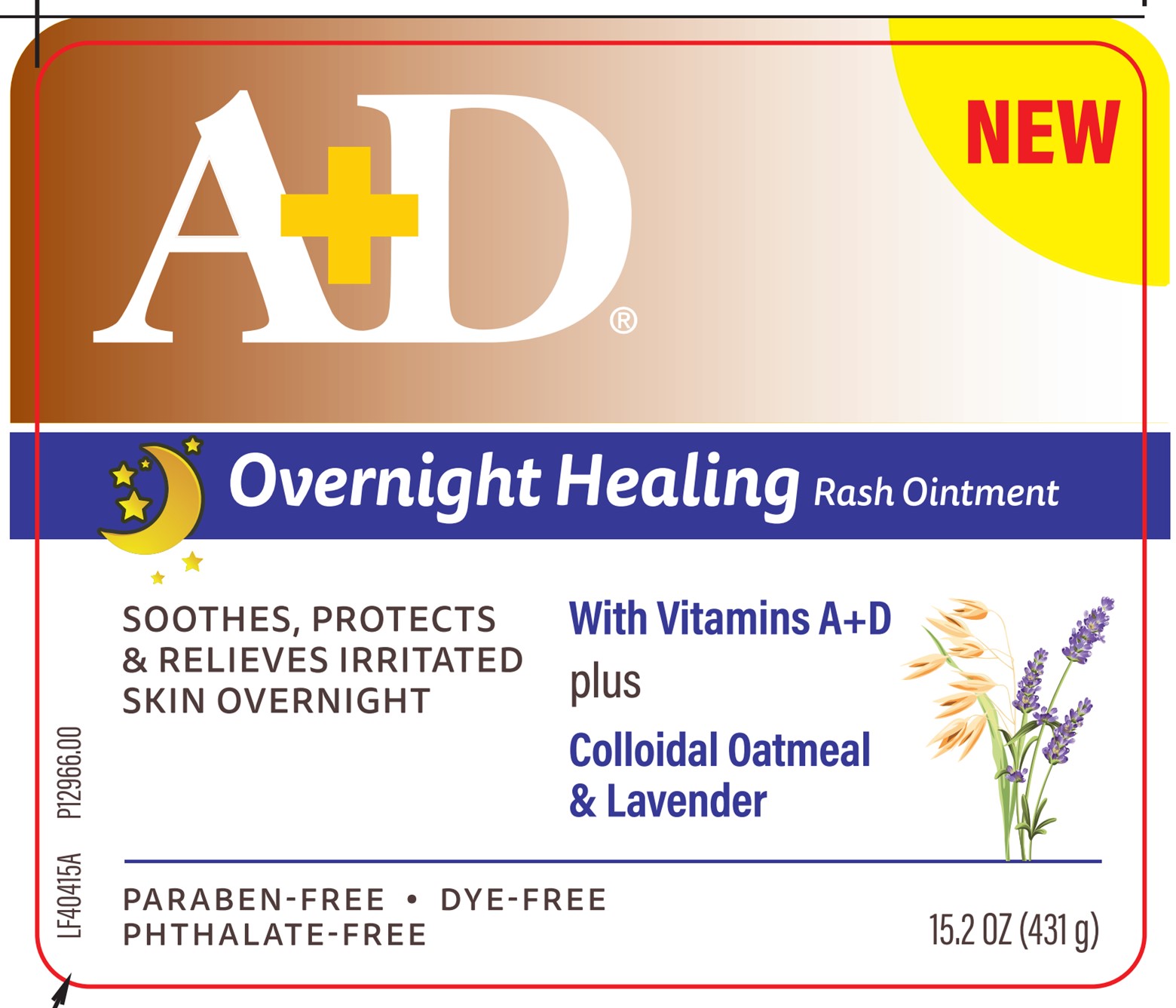 DRUG LABEL: AD Overnight Healing
NDC: 65197-404 | Form: OINTMENT
Manufacturer: WellSpring Pharmaceutical Corporation
Category: otc | Type: HUMAN OTC DRUG LABEL
Date: 20250108

ACTIVE INGREDIENTS: PETROLATUM 47.2 g/100 g
INACTIVE INGREDIENTS: ACETOIN; BENZALDEHYDE; CALENDULA OFFICINALIS FLOWER; CAMPHOR (SYNTHETIC); CANDELILLA WAX; COD LIVER OIL; EUCALYPTUS OIL; CHAMOMILE; GERANIUM OIL, ALGERIAN TYPE; GLYCERIN; LANOLIN; LIGHT MINERAL OIL; MICROCRYSTALLINE WAX; LAVENDER OIL; MINERAL OIL; OATMEAL; PARAFFIN; POTASSIUM SORBATE; SORBIC ACID; WATER

A+D OVERNIGHT HEALING Rash Ointment

Active Ingredients

Petrolatum 47.2%

Purpose

Skin protectant

Uses

- helps treat and prevent diaper rash
- protects minor skin irritation due to diaper rash and helps seal out wetness
- helps prevent and temporarily protects chafed, chapped or cracked skin

Warnings

For external use only

When using this product

- do not get into eyes
- do not apply over raw surfaces or blistered areas

Stop use and ask a doctor if

- condition worsens
- symptoms persist for more than 7 days, or clear up and occur again within a few days

Keep out of reach of children

If swallowed, get medical help or contact a Poison Control Center right away.

Directions

- apply as needed
- change wet and soiled diapers promptly
- cleanse the diaper area, and allow to dry
- apply ointment liberally as often as necessary, with each diaper change, especially at bedtime or anytime when exposure to wet diapers may be prolonged

Other information

store between 20° to 25°C (68° to 77°F)

Inactive ingredients

Acetyl Methyl Carbinol, Avena Sativa (Oat) Kernel Flour, Benzaldehyde, Calendula Officinalis Flower Extract, Camphor, Chamomilla Recutita (Matricaria) Flower Extract, Cod Liver Oil (contains vitamin A & vitamin D), Eucalyptus Oil, Euphorbia Cerifera (Candelilla) Wax, Fragrance (Parfum), Geranium Oil, Glycerin, Lanolin, Lavender Oil, Light Mineral Oil, Microcrystalline Wax, Paraffin, Potassium Sorbate, Sorbic Acid, Water, White Mineral Oil.

Questions?

1-844-241-5454

Distributed by:

WellSpring Pharmaceutical Corporation
Sarasota, FL 34243

© 2024 WellSpring Pharmaceutical Corporation

www.ADskinhealth.com

PACKAGE LABEL. PRINCIPAL DISPLAY PANEL 65197-404-04

A+D OVERNIGHT HEALING Rash Ointment

Soothes, Protects & Relieves Irritated Skin Overnight

WITH VITAMIN A & VITAMIN D plus COLLOIDAL OATMEAL & LAVENDER

PARABEN-FREE
DYE-FREE
PHTHALATE-FREE

NET WT 3.6 OZ (102g)

Skin nourishing formula with Vitamin A and Vitamin D

helps heal and moisturize irritated skin

helps repair and rejuvenate aggravated skin

Use A+D Overnight Healing on:

Bum
Legs
Hands
Cheeks
Neck Knees
Elbows Feet

Clinically Shown to Improve

Redness

Dryness

Itching

Diaper Rash

Irritated Skin

CT40400B

P12842.00

NDC# 65197-404-04

AD Overnight Healing 3.6oz

65197-404-15

A+D OVERNIGHT HEALING Rash Ointment

Soothes, Protects & Relieves Irritated Skin Overnight

WITH VITAMIN A & VITAMIN D plus COLLOIDAL OATMEAL & LAVENDER

PARABEN-FREE
DYE-FREE
PHTHALATE-FREE

NET WT 15.2 OZ (431g)

Skin nourishing formula with Vitamin A and Vitamin D

helps heal and moisturize irritated skin

helps repair and rejuvenate aggravated skin

Use A+D Overnight Healing on:

Bum
Legs
Hands
Cheeks
Neck Knees
Elbows Feet

Clinically Shown to Improve

Redness

Dryness

Itching

Diaper Rash

Irritated Skin

LF40415A

P12966.00

NDC# 65197-404-15

Overnight 15.2 oz